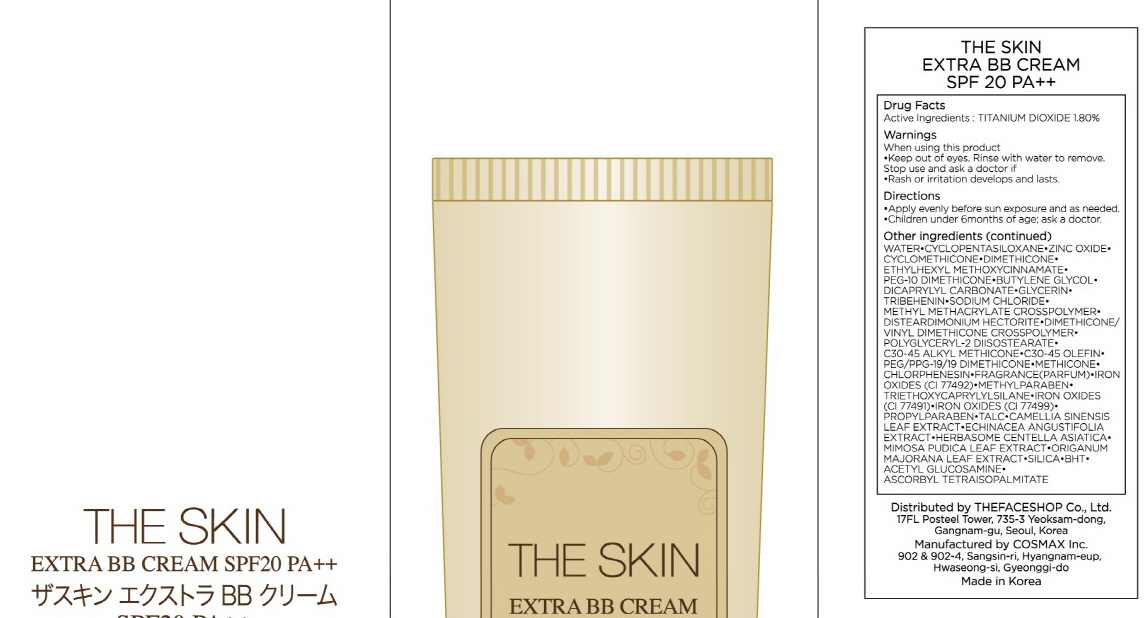 DRUG LABEL: THE SKIN EXTRA BB
NDC: 51523-025 | Form: CREAM
Manufacturer: THEFACESHOP CO., LTD.
Category: otc | Type: HUMAN OTC DRUG LABEL
Date: 20100714

ACTIVE INGREDIENTS: TITANIUM DIOXIDE 0.81 g/45 g

Drug Facts

Active Ingredient: TITANIUM DIOXIDE

Inactive Ingredients:
WATER, CYCLOPENTASILOXANE, ZINC OXIDE, CYCLOMETHICONE, DIMETHICONE, ETHYLHEXYL METHOXYCINNAMATE, PEG-10 DIMETHICONE, BUTYLENE GLYCOL, DICAPRYLYL CARBONATE, GLYCERIN, TRIBEHENIN, SODIUM CHLORIDE, METHYL METHACRYLATE CROSSPOLYMER, DISTEARDIMONIUM HECTORITE, DIMETHICONE/VINYL DIMETHICONE CROSSPOLYMER, POLYGLYCERYL-2 DIISOSTEARATE, C30-45 ALKYL METHICONE, C30-45 OLEFIN, PEG/PPG-19/19 DIMETHICONE, METHICONE, CHLORPHENESIN, FRAGRANCE, IRON OXIDES(CI 77492), METHYLPARABEN, TRIETHOXYCAPRYLYLSILANE, IRON OXIDES(CI 77491), IRON OXIDES(CI 77499), PROPYLPARABEN, TALC, CAMELLIA SINENSIS LEAF EXTRACT, ECHINACEA ANGUSTIFOLIA EXTRACT, HERBASOME CENTELLA ASIATICA, MIMOSA PUDICA LEAF EXTRACT, ORIGANUM MAJORANA LEAF EXTRACT, SILICA, BHT, ACETYL GLUCOSAMINE, ASCORBYL TETRAISOPALMITATE

Warnings:
When using this product
Keep out of eyes. Rinse with water to remove.
Stop use and ask a doctor if
Rash or irritation develops and lasts.
Directions:
Apply evenly before sun exposure and as needed.
Children under 6months of age; ask a doctor.